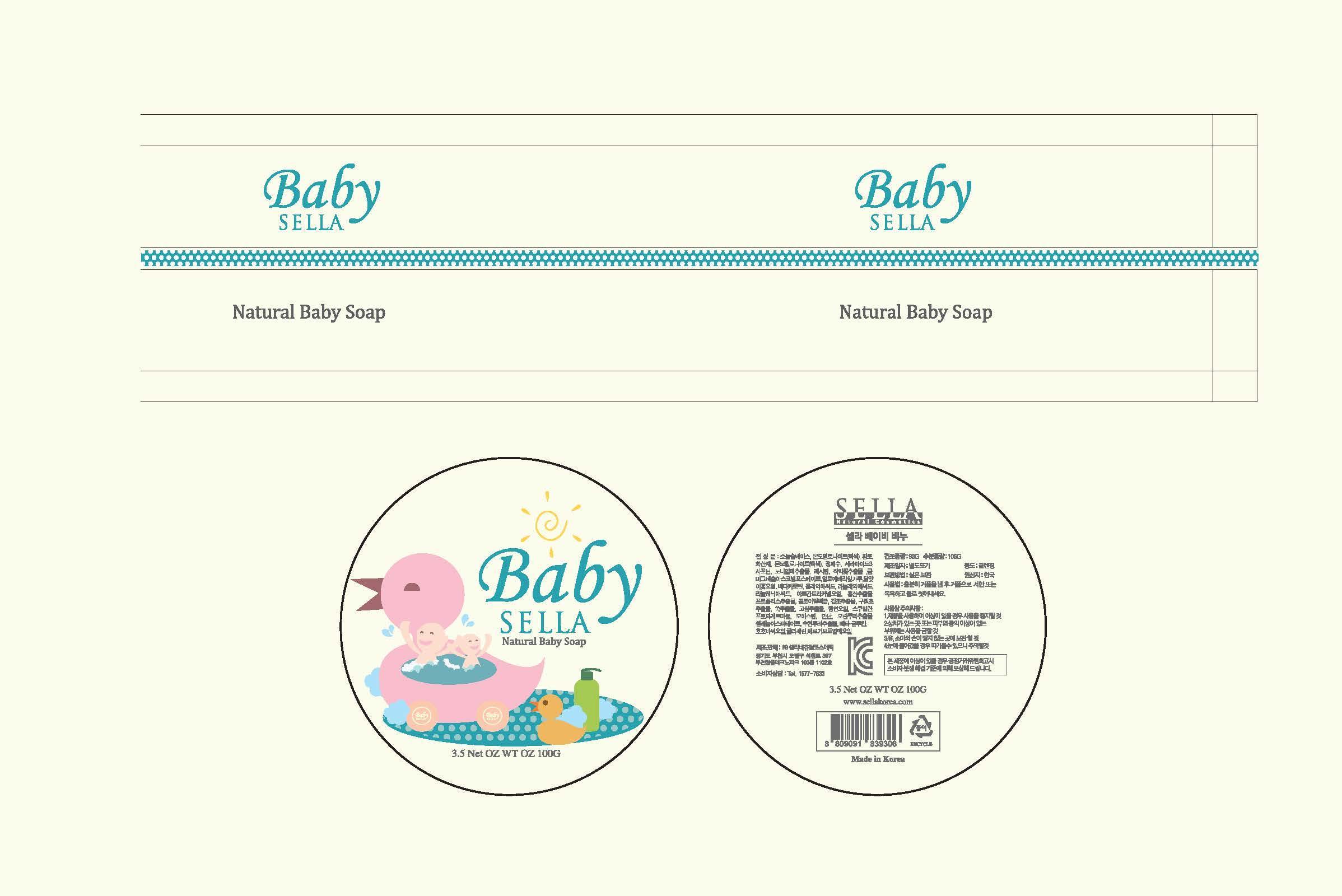 DRUG LABEL: SELLA NATURAL BABY
NDC: 69603-0701 | Form: SOAP
Manufacturer: Sella Natural Cosmetics Co.,Ltd.
Category: otc | Type: HUMAN OTC DRUG LABEL
Date: 20150211

ACTIVE INGREDIENTS: GLYCERIN 0.5 g/100 g
INACTIVE INGREDIENTS: LINOLEIC ACID; SQUALENE; GLYCYRRHIZA GLABRA

Drug Facts

ACTIVE INGREDIENT

glycerine

INACTIVE INGREDIENT

oleic acid, linoleic acid, water, squalene, lecithin etc

PURPOSE

skin protectant

keep out of reach of the children

INDICATIONS AND USAGE

massage with soapsuds, then cleanse gently

WARNINGS

・Stop using the product when you have skin problems or the product disagrees with your skin
・Stop using the product immediately and consult a dermatologist if you have redness, swelling, itching or irritation on the skin while or after using the product.
・Don't place the product in any place where it will be subjected to extremely high or low temperatures or direct sunlight.

DOSAGE AND ADMINISTRATION

for external use only